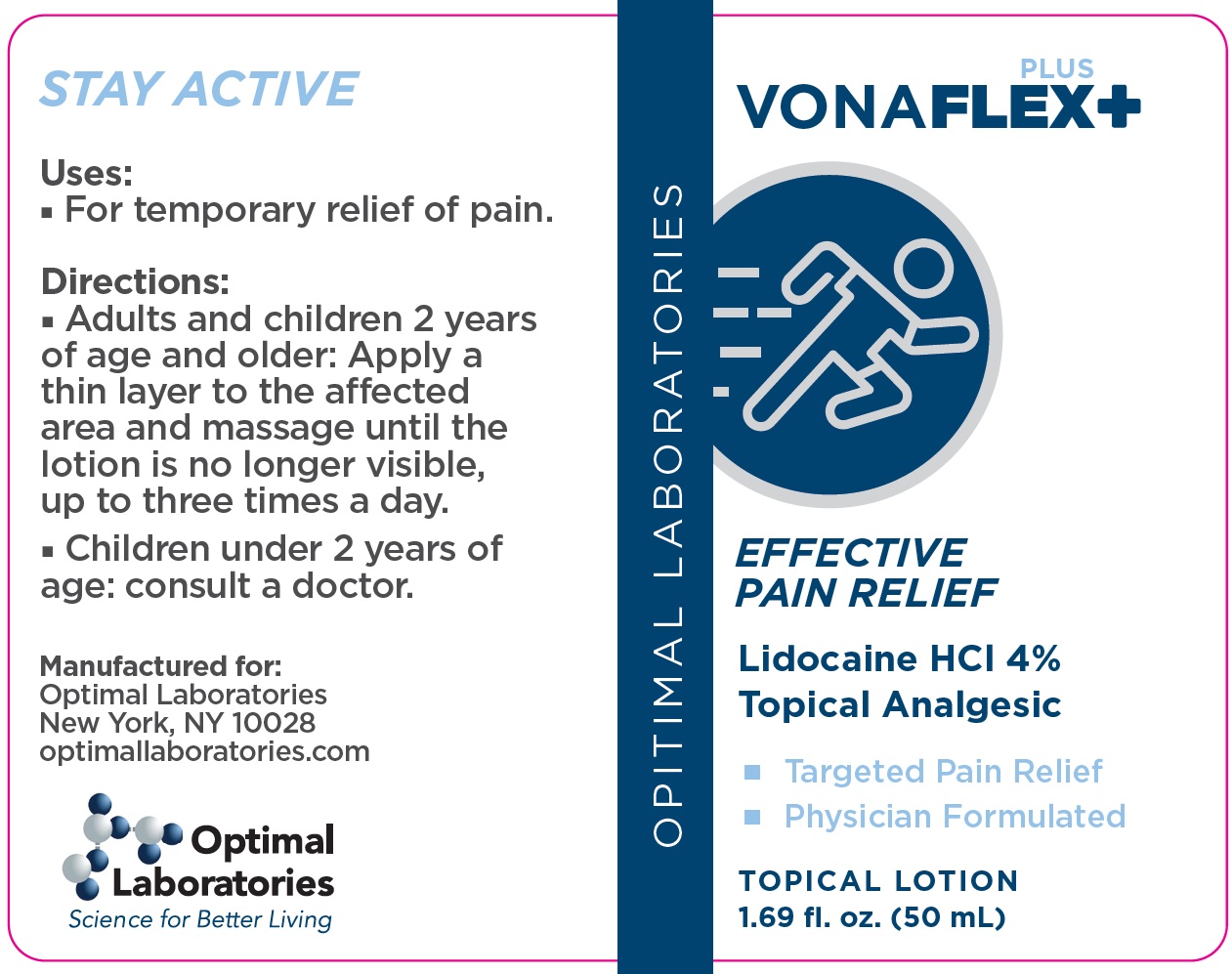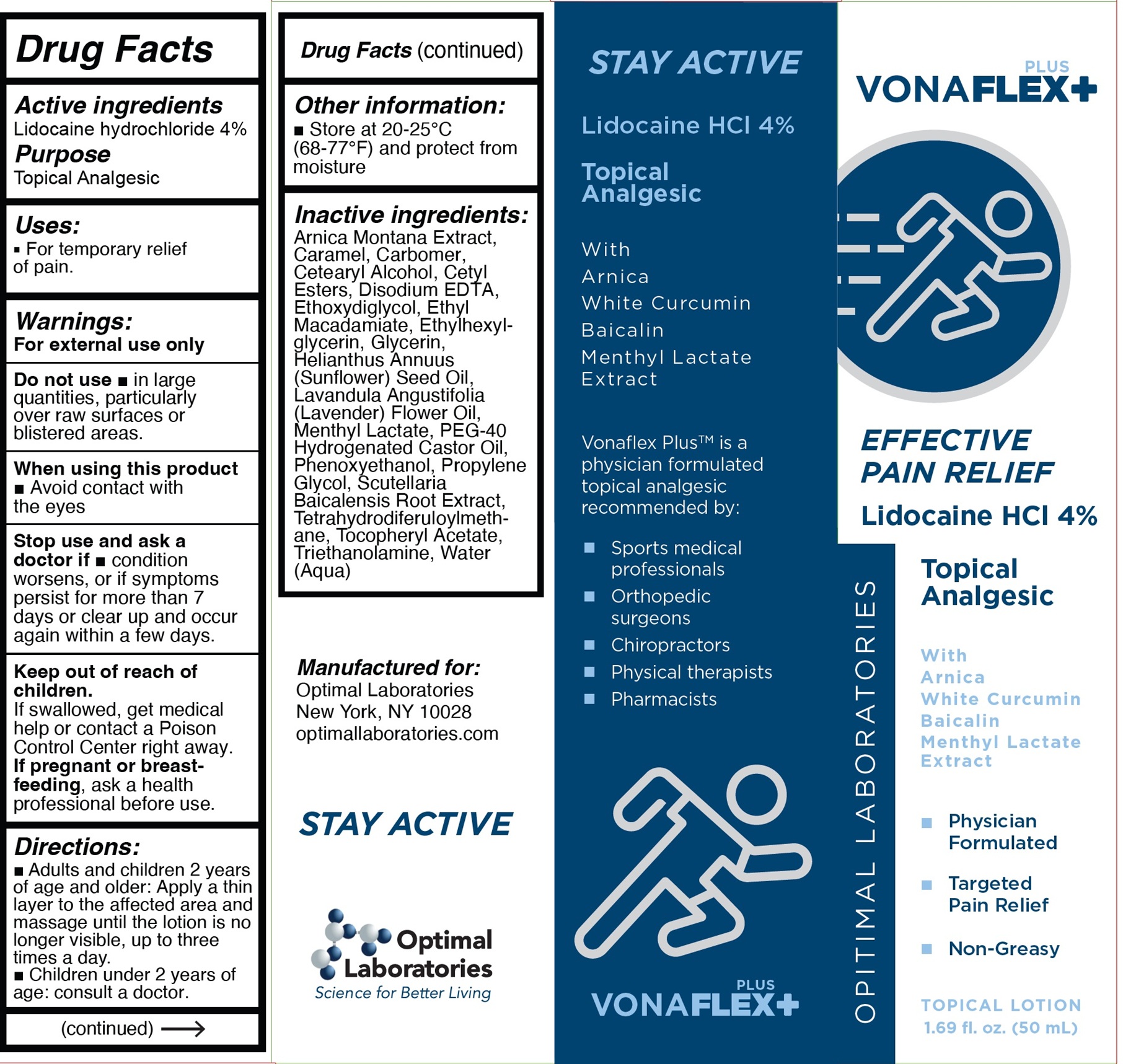 DRUG LABEL: VonaFlex Effective Pain Relief Topical Analgesic
NDC: 87359-987 | Form: CREAM
Manufacturer: OPTIMAL LABORATORIES, LLC
Category: otc | Type: HUMAN OTC DRUG LABEL
Date: 20260128

ACTIVE INGREDIENTS: LIDOCAINE HYDROCHLORIDE 40 mg/1 mL
INACTIVE INGREDIENTS: ARNICA MONTANA WHOLE; CARAMEL; CARBOMER HOMOPOLYMER, UNSPECIFIED TYPE; CETOSTEARYL ALCOHOL; CETYL ESTERS WAX; EDETATE DISODIUM; DIETHYLENE GLYCOL MONOETHYL ETHER; ETHYL MACADAMIATE; ETHYLHEXYLGLYCERIN; GLYCERIN; SUNFLOWER OIL; MENTHYL LACTATE, (-)-; POLYOXYL 40 HYDROGENATED CASTOR OIL; PHENOXYETHANOL; PROPYLENE GLYCOL; SCUTELLARIA BAICALENSIS ROOT; TETRAHYDRODIFERULOYLMETHANE; .ALPHA.-TOCOPHEROL ACETATE; TROLAMINE; WATER

VonaFlex+ Effective Pain Relief Topical Analgesic

Active ingredients

Lidocaine hydrochloride 4%

Purpose

Topical Analgesic

Uses:

- For temporary relief of pain

Warnings:

For external use only

Do not use

- in large quantities, particularly over raw surfaces or blistered areas

When using this product

- Avoid contact with the eyes

Stop use and ask a doctor if

- condition worsens, or if symptoms persist for more than 7 days or clear up and occur again within a few days.

Keep out of reach of children.

If swallowed, get medical help or contact a Poison Control Center right away.

If pregnant or breast-feeding,

ask a health professional before use.

Directions:

- Adults and children 2 years of age and older: Apply a thin layer to the affected area and massage until the lotion is no longer visible, up to three times a day.
- Children under 2 years of age: consult a doctor.

Other information:

- Store at 20-25°C (68-77°F) and protect from moisture

Inactive ingredients:

Arnica Montana Extract, Caramel, Carbomer, Cetearyl Alcohol, Cetyl Esters, Disodium EDTA, Ethoxydiglycol, Ethyl Macadamiate, Ethylhexylglycerin, Glycerin, Helianthus Annuus (Sunflower) Seed Oil, Lavandula Angustifolia (Lavender) Flower Oil, Menthyl Lactate, PEG-40 Hydrogenated Castor Oil, Phenoxyethanol, Propylene Glycol, Scutellaria Baicalensis Root Extract, Tetrahydrodiferuloylmethane, Tocopheryl Acetate, Triethanolamine, Water (Aqua)